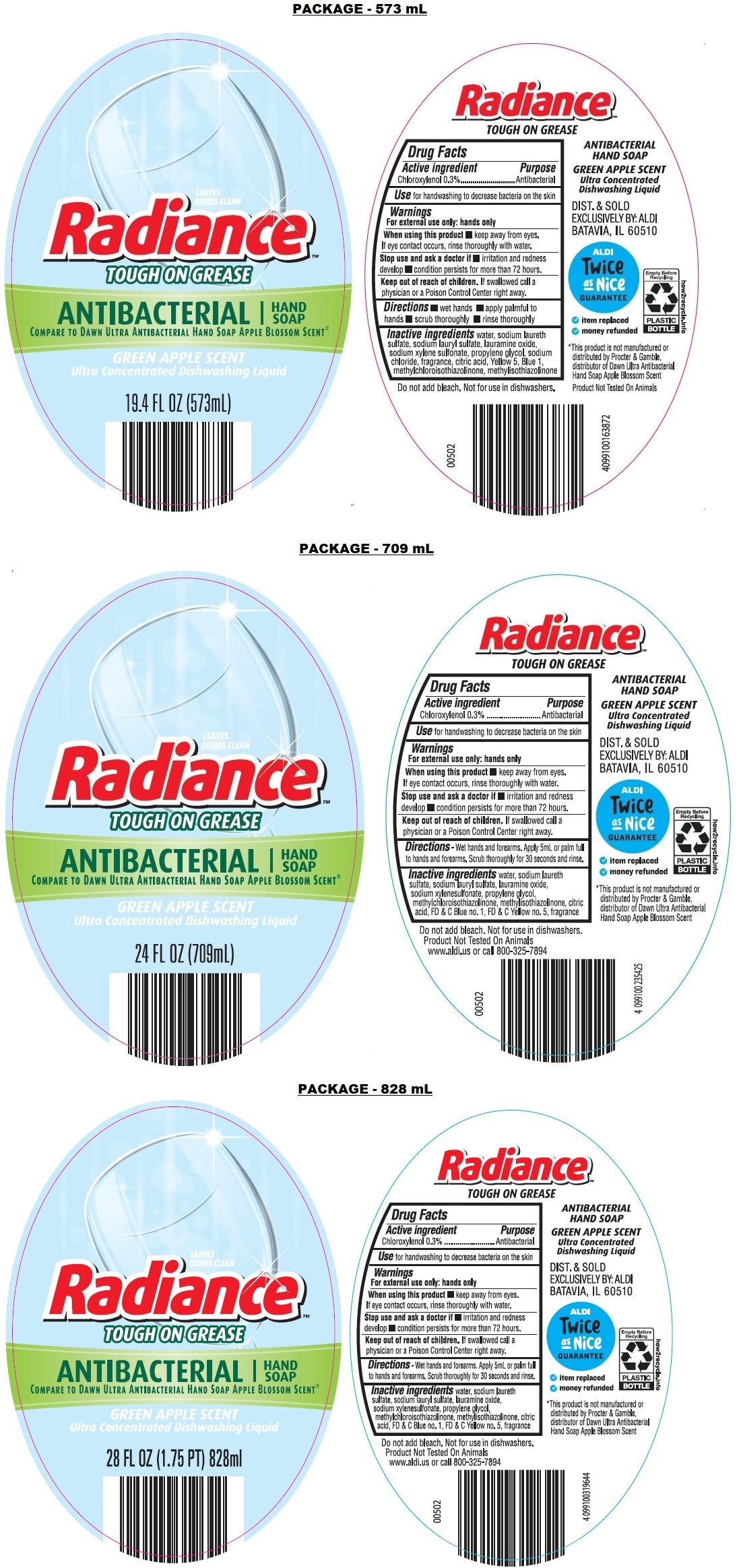 DRUG LABEL: Radiance Antibacterial Green Apple Scent Hand
NDC: 73487-003 | Form: SOAP
Manufacturer: Korex Chicago LLC
Category: otc | Type: HUMAN OTC DRUG LABEL
Date: 20251215

ACTIVE INGREDIENTS: CHLOROXYLENOL 0.3 g/100 mL
INACTIVE INGREDIENTS: WATER; SODIUM LAURETH-3 SULFATE; SODIUM LAURYL SULFATE; LAURAMINE OXIDE; SODIUM XYLENESULFONATE; PROPYLENE GLYCOL; METHYLCHLOROISOTHIAZOLINONE; METHYLISOTHIAZOLINONE; CITRIC ACID MONOHYDRATE; FD&C BLUE NO. 1; FD&C YELLOW NO. 5

Radiance Antibacterial Hand Soap Green Apple Scent 73487-003

Active ingredient

Chloroxylenol 0.3%

Purpose

Antibacterial

Use

for handwashing to decrease bacteria on the skin

Warnings

For external use only: hands only

When using this product • keep away from eyes. If eye contact occurs, rinse thoroughly with water.

Stop use and ask a doctor if • irritation and redness develop • condition persists for more than 72 hours.

Keep out of reach of children. If swallowed call a physician or a Poison Control Center right away.

Directions

- Wet hands and forearms. Apply 5mL or palm full to hands and forearms. Scrub thoroughly for 30 seconds and rinse.

Inactive ingredients

water, sodium laureth sulfate, sodium lauryl sulfate, lauramine oxide, sodium xylenesulfonate, propylene glycol, methylchloroisothiazolinone, methylisothiazolinone, citric acid, FD & C Blue no. 1, FD & C Yellow no. 5, fragrance.

LEAVES DISHES CLEAN

TOUGH ON GREASE

COMPARE TO DAWN ULTRA ANTIBACTERIAL HAND SOAP APPLE BLOSSOM SCENT*.

GREEN APPLE SCENT

Ultra Concentrated Dishwashing Liquid

DIST. & SOLD EXCLUSIVELY BY: ALDI BATAVIA, IL 60510

ALDI Twice as Nice GUARANTEE

- i tem replaced
- money refunded

*This product is not manufactured or distributed by Procter & Gamble, distributor of Dawn Ultra Antibacterial Hand Soap Apple Blossom Scent

Do not add bleach. Not for use in dishwashers.

Product Not Tested On Animals.

www.aldi.us or call 800-325-7894